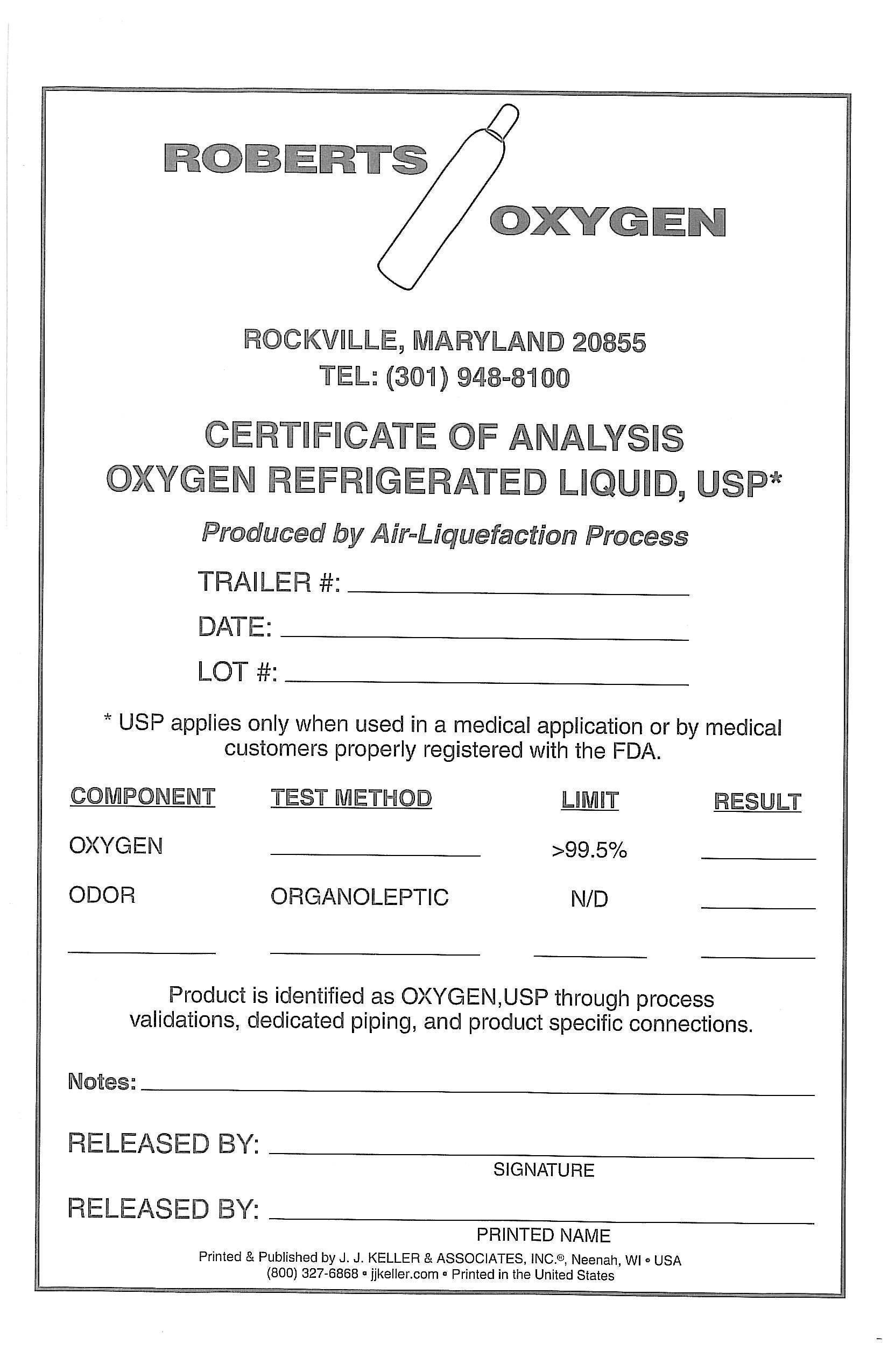 DRUG LABEL: Oxygen
NDC: 46123-045 | Form: GAS
Manufacturer: Roberts Oxygen Company, Inc.
Category: prescription | Type: HUMAN PRESCRIPTION DRUG LABEL
Date: 20251117

ACTIVE INGREDIENTS: OXYGEN 990 mL/1 L

OXYGEN REFRIGERATED LIQUID, USP-045

PACKAGE LABEL

ROBERTS OXYGEN
ROCKVILLE, MARYLAND 20866
TEL: (301) 948-8100

CERTIFICATE OF ANALYSIS
OXYGEN REFRIGERATED LIQUID, USP*

PRODUCED BY AIR-LIQUEFACTION PROCESS

TRAILER#: ______________

DATE: _________________

LOT#: _________________

*USP applies only when used in a medical application or by medical customers properly registered with the FDA.

Component Test Method Limit Result

Oxygen ______ >99.5% _______

Odor ORGANOLEPTIC N/D ______

________ _________ _________ _________

Product is identified as OXYGEN, USP through process validations, dedicated piping, and product specific connections.

Notes: _____________________________________

RELEASED BY: ____________________________

SIGNATURE

RELEASED BY: ____________________________

PRINTED NAME

Printed & Published by J.J. KELLER & ASSPCIATES, INC., Neenah, WI * USP

(800) 327-6868 *jjkeller.com * Printer in the Unitied States